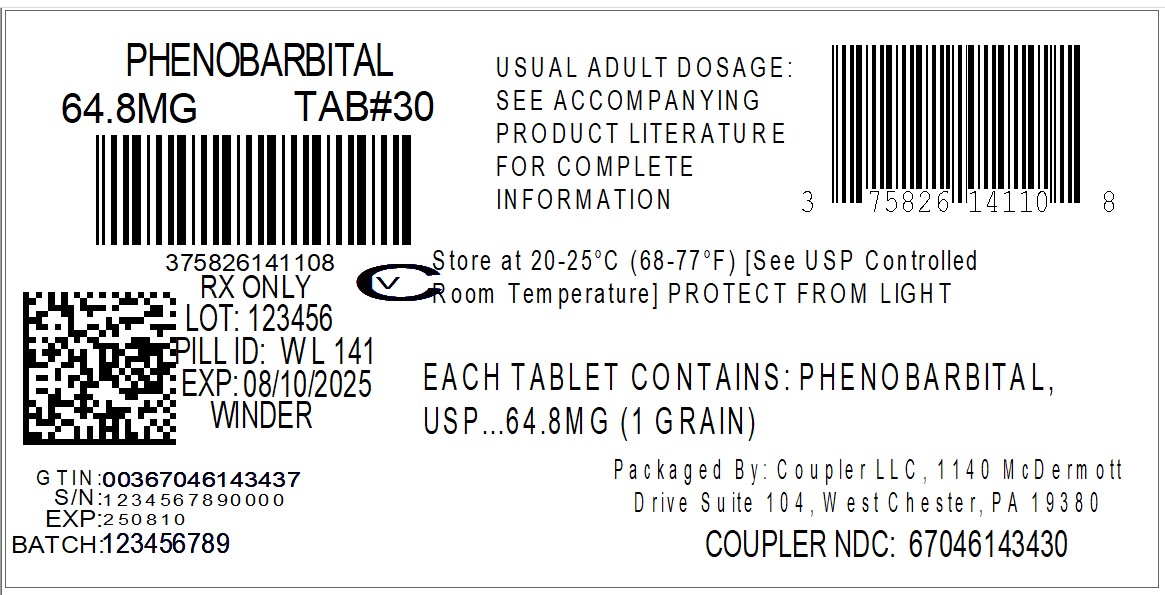 DRUG LABEL: Phenobarbital
NDC: 67046-1434 | Form: TABLET
Manufacturer: Coupler LLC
Category: prescription | Type: HUMAN PRESCRIPTION DRUG LABEL
Date: 20250702
DEA Schedule: CIV

ACTIVE INGREDIENTS: PHENOBARBITAL 64.8 mg/1 1
INACTIVE INGREDIENTS: LACTOSE MONOHYDRATE; CELLULOSE, MICROCRYSTALLINE; SODIUM STARCH GLYCOLATE TYPE A POTATO; SILICON DIOXIDE; MAGNESIUM STEARATE

PHENOBARBITAL TABLETS, USP CIV
Rx Only
Rev. Jan 2022

DESCRIPTION

The barbiturates are nonselective central nervous system (CNS) depressants primarily used as sedative-hypnotics. In subhypnotic doses, they are also used as anticonvulsants. The barbiturates and their sodium salts are subject to control under the Federal Controlled Substances Act.

Phenobarbital is a barbituric acid derivative for oral administration and occurs as a white, odorless, slightly bitter powder that is soluble in chloroform, freely soluble in alcohol or ether, and slightly soluble in water. Its saturated solution has a pH of about 5.6. Chemically, it is 5-ethyl-5-phenylbarbituric acid with the molecular formula C12H12N2O3(232.24).

The structural formula is as follows:

Each Phenobarbital Tablet, USP contains 15 mg, 16.2 mg, 30 mg, 32.4 mg, 60 mg, 64.8 mg, 97.2 mg, or 100 mg of phenobarbital, USP.

Inactive ingredients are as follows:

Microcrystalline Cellulose; Lactose Monohydrate; Sodium Starch Glycolate, Type-A; Colloidal Silicon Dioxide; Magnesium Stearate

CLINICAL PHARMACOLOGY

Phenobarbital, a long-acting barbiturate, is a central nervous system depressant. In ordinary doses, the drug acts as a sedative and anticonvulsant. Its onset of action occurs within 30 minutes, and the duration of action ranges from 5 to 6 hours. It is detoxified in the liver.

INDICATIONS AND USAGE

Phenobarbital Tablets, USP are indicated for use as a sedative or anticonvulsant.

CONTRAINDICATIONS

Phenobarbital is contraindicated in patients who are hypersensitive to barbiturates. In such patients, severe hepatic damage can occur from ordinary doses and is usually associated with dermatitis and involvement of parenchymatous organs. A personal or familial history of acute intermittent porphyria represents one of the few absolute contraindications to the use of barbiturates. Phenobarbital is also contraindicated in patients with marked impairment of liver function, or respiratory disease in which dyspnea or obstruction is evident. It should not be administered to persons with known previous addiction to the sedative/hypnotic group, since ordinary doses may be ineffectual and may contribute to further addiction.

WARNINGS

In small doses, the barbiturates may increase the reaction to painful stimuli. Taken by themselves, the barbiturates cannot be relied upon to relieve pain or even to produce sedation or sleep in the presence of severe pain.

PRECAUTIONS

General Precautions

Barbiturates induce liver microsomal enzyme activity. This accelerates the biotransformation of various drugs and is probably part of the mechanism of the tolerance encountered with barbiturates.

Phenobarbital, therefore, should be used with caution in patients with decreased liver function. This drug should also be administered cautiously to patients with a history of drug dependence or abuse (see DRUG ABUSE AND DEPENDENCE).

Phenobarbital may decrease the potency of coumarin anticoagulants; therefore, patients receiving such concomitant therapy should have more frequent prothrombin determinations. As with other sedatives and hypnotics, elderly or debilitated patients may react to barbiturates with marked excitement, depression, or confusion.

The systemic effects of exogenous hydrocortisone and endogenous hydrocortisone (cortisol) may be diminished by phenobarbital. Thus, this product should be administered with caution to patients with borderline hypoadrenal function, regardless of whether it is of pituitary or of primary adrenal origin.

Information for Patients

Phenobarbital may impair the mental and/or physical abilities required for the performance of potentially hazardous tasks, such as driving a car or operating machinery. The patient should be cautioned accordingly.

Drug Interactions

Phenobarbital in combination with alcohol, tranquilizers, and other central nervous system depressants has additive depressant effects, and the patient should be so advised. Patients taking this drug should be warned not to exceed the dosage recommended by their physician. Toxic effects and fatalities have occurred following overdoses of phenobarbital alone and in combination with other central nervous system depressants. Caution should be exercised in prescribing unnecessarily large amounts of phenobarbital for patients who have a history of emotional disturbances or suicidal ideation or who have misused alcohol and other CNS drugs (see OVERDOSAGE).

Usage in Pregnancy

Pregnancy Category B

Reproduction studies have been performed in animals and have revealed no evidence of impaired fertility or harm to the fetus due to phenobarbital. There are, however, no adequate and well-controlled studies in pregnant women. Because animal reproduction studies are not always predictive of human response, this drug should be used during pregnancy only if clearly needed and under the supervision of a physician .

Nursing Mothers

Caution should be exercised when phenobarbital is administered to a nursing woman.

ADVERSE REACTIONS

The following adverse reactions have been reported:

CNS Depression:

Residual sedation or "hangover," drowsiness, lethargy, and vertigo. Emotional disturbances and phobias may be accentuated. In some persons, barbiturates such as phenobarbital repeatedly produce excitement rather than depression, and the patient may appear to be inebriated. Like other nonanalgesic hypnotic drugs, barbiturates, such as phenobarbital, when given in the presence of pain, may cause restlessness, excitement, and even delirium. Rarely, the use of barbiturates results in localized or diffused myalgic, neuralgic, or arthritic pain, especially in psychoneurotic patients with insomnia. The pain may appear in paroxysms, is most intense in the early morning hours, and is most frequently located in the region of the neck, shoulder girdle, and upper limbs. Symptoms may last for days after the drug is discontinued.

Respiratory/Circulatory:

Respiratory depression, apnea, circulatory collapse.

Allergic:

Acquired hypersensitivity to barbiturates consists chiefly in allergic reactions that occur especially in persons who tend to have asthma, urticaria, angioedema, and similar conditions. Hypersensitivity reactions in this category include localized swelling, particularly of the eyelids, cheeks, or lips, and erythematous dermatitis. Rarely, exfoliative dermatitis (e.g., Stevens-Johnson syndrome and toxic epidermal necrolysis) may be caused by phenobarbital and can prove fatal. The skin eruption may be associated with fever, delirium, and marked degenerative changes in the liver and other parenchymatous organs. In a few cases, megaloblastic anemia has been associated with the chronic use of phenobarbital.

Other:

Nausea and vomiting; headache.

To report SUSPECTED ADVERSE REACTIONS, contact Winder Laboratories, LLC at 1-770-307-0703, or FDA at 1-800-FDA-1088 or www.fda.gov/medwatch.

DRUG ABUSE AND DEPENDENCE

Controlled Substance

Phenobarbital is a Schedule IV drug.

Dependence

Prolonged, uninterrupted use of barbiturates (particularly the short-acting drugs), even in therapeutic doses, may result in psychic and physical dependence. Withdrawal symptoms due to physical dependence following chronic use of large doses of barbiturates may include delirium, convulsions, and death.

OVERDOSAGE

The signs and symptoms of barbiturate poisoning are referable especially to the central nervous system and the cardiovascular system. Moderate intoxication resembles alcoholic inebriation. In severe intoxication, the patient is comatose, the level of reflex activity conforming in a general way to the intensity of the central depression. The deep reflexes may persist for some time despite coexistent coma. The Babinski sign is often positive. The EEG may be of the "burst-suppression" type, with brief periods of electrical silence. The pupils may be constricted and react to light, but late in the course of barbiturate poisoning they may show hypoxic paralytic dilatation. Respiration is affected early.

Breathing may be either slow or rapid and shallow; Cheyne-Stokes rhythm may be present. Respiratory minute volume is diminished, and hypoxia and respiratory acidosis may develop. The blood pressure falls, owing partly to depression of medullary vasomotor centers; partly to a direct action of the drug on the myocardium, sympathetic ganglia, and vascular smooth muscle; partly to hypoxia.

The patient thus develops a typical shock syndrome, with a weak and rapid pulse, cold and clammy skin, and a rise in the hematocrit. Respiratory complications (atelectasis, pulmonary edema, and bronchopneumonia) and renal failure are much dreaded and not infrequent concomitant of severe barbiturate poisoning. There is usually hypothermia, sometimes with temperatures as low as 32°C.

Treatment

General management should consist of symptomatic and supportive therapy, including gastric lavage, administration of intravenous fluids, and maintenance of blood pressure, body temperature and adequate respiratory exchange. Dialysis will increase the rate of removal of barbiturates from the body fluids. Antibiotics may be required to control pulmonary complications.

DOSAGE AND ADMINISTRATION

Oral Sedative Dose, Adults:30 to 120 mg daily in 2 or 3 divided doses.

Children:6 mg/kg of body weight daily in 3 divided doses.

Oral Hypnotic Dose, Adults:100 to 320 mg.

Oral Anticonvulsant Dose, Adults:50 to 100 mg 2 or 3 times daily.

Children:15 to 50 mg 2 or 3 times daily.

HOW SUPPLIED

Phenobarbital Tablets, USP 15 mg:

White, Round Tablet; Debossed WL on one side and 136 on the other side.

Bottles of 90 tablets | NDC 75826-136-90
Bottles of 100 tablets | NDC 75826-136-10
Bottles of 500 tablets | NDC 75826-136-50
Bottles of 1000 tablets | NDC 75826-136-00

Phenobarbital Tablets, USP 16.2 mg (¼ grain):

White, Round, Scored Tablet; Debossed WL on one side and 137 on the other side.

Bottles of 90 tablets | NDC 75826-137-90
Bottles of 100 tablets | NDC 75826-137-10
Bottles of 500 tablets | NDC 75826-137-50
Bottles of 1000 tablets | NDC 75826-137-00

Phenobarbital Tablets, USP 30 mg:

White, Round, Scored Tablet; Debossed WL on one side and 138 on the other side.

Bottles of 90 tablets | NDC 75826-138-90
Bottles of 100 tablets | NDC 75826-138-10
Bottles of 500 tablets | NDC 75826-138-50
Bottles of 1000 tablets | NDC 75826-138-00

Phenobarbital Tablets, USP 32.4 mg (½ grain):

White, Round, Scored Tablet; Debossed WL on one side and 139 on the other side.

Bottles of 90 tablets | NDC 75826-139-90
Bottles of 100 tablets | NDC 75826-139-10
Bottles of 500 tablets | NDC 75826-139-50
Bottles of 1000 tablets | NDC 75826-139-00

Phenobarbital Tablets, USP 60 mg:

White, Round Tablet; Debossed WL on one side and 140 on the other side.

Bottles of 90 tablets | NDC 75826-140-90
Bottles of 100 tablets | NDC 75826-140-10
Bottles of 500 tablets | NDC 75826-140-50
Bottles of 1000 tablets | NDC 75826-140-00

Phenobarbital Tablets, USP 64.8 mg (1 grain):

White, Round, Scored Tablet; Debossed WL on one side and 141 on the other side.

Bottles of 90 tablets | NDC 75826-141-90
Bottles of 100 tablets | NDC 75826-141-10
Bottles of 500 tablets | NDC 75826-141-50
Bottles of 1000 tablets | NDC 75826-141-00

Phenobarbital Tablets, USP 97.2 mg (1½ grain):

White, Round, Scored Tablet; Debossed WL on one side and 142 on the other side.

Bottles of 90 tablets | NDC 75826-142-90
Bottles of 100 tablets | NDC 75826-142-10
Bottles of 500 tablets | NDC 75826-142-50
Bottles of 1000 tablets | NDC 75826-142-00

Phenobarbital Tablets, USP 100 mg:

White, Round, Scored Tablet; Debossed WL on one side and 143 on the other side.

Bottles of 90 tablets | NDC 75826-143-90
Bottles of 100 tablets | NDC 75826-143-10
Bottles of 500 tablets | NDC 75826-143-50
Bottles of 1000 tablets | NDC 75826-143-00

STORAGE AND HANDLING

Store at 20° to 25°C (68° to 77°F) [See USP Controlled Room Temperature]. Protect from light and moisture.

Dispense in a tight, light-resistant container as defined in the USP using a child-resistant closure.

Manufactured by:
Winder Laboratories, LLC.
Winder, GA 30680
RLS.135.99-1.0
Updated: Jan 2022